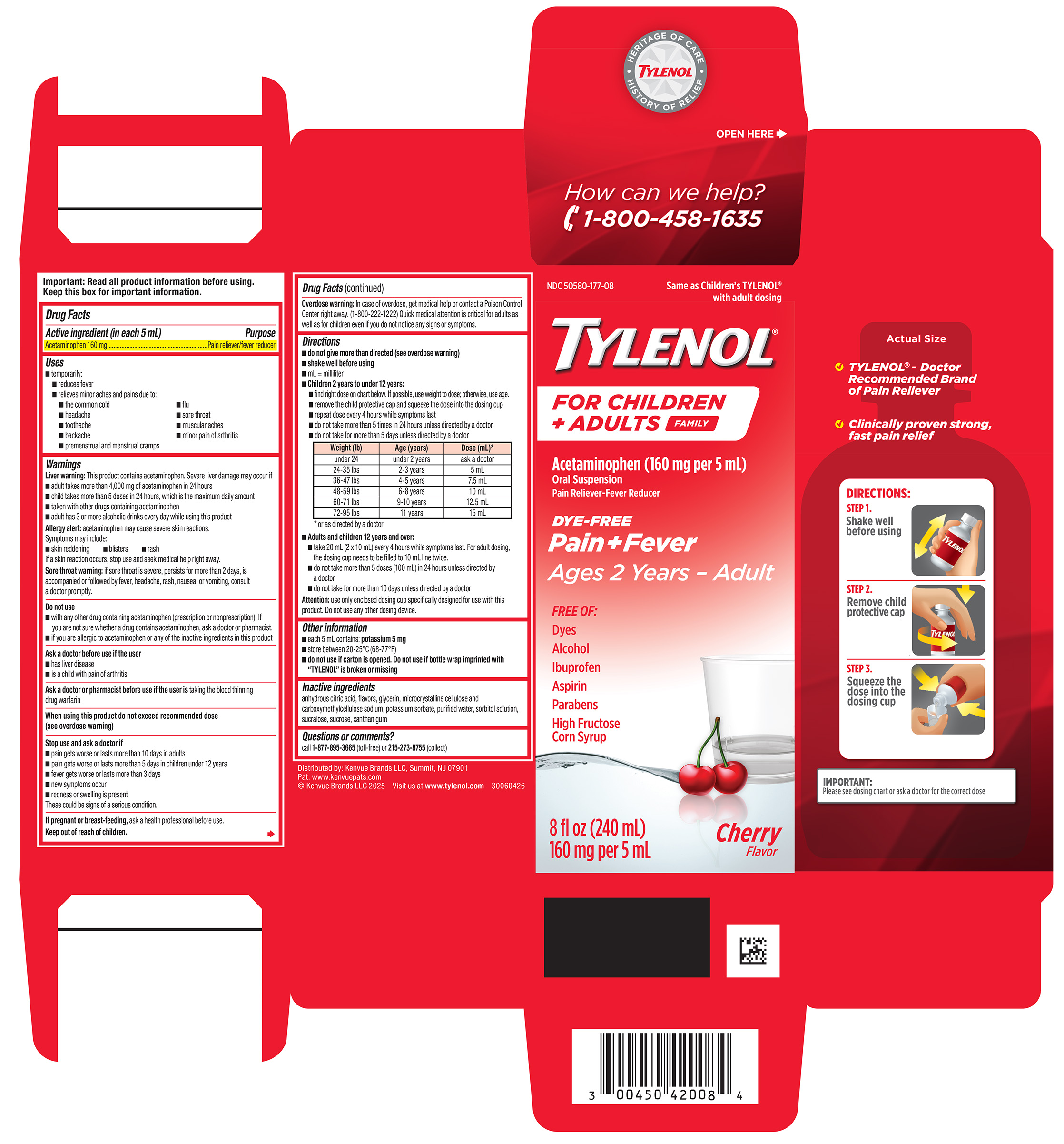 DRUG LABEL: TYLENOL For Children Plus Adults
NDC: 50580-177 | Form: SUSPENSION
Manufacturer: Kenvue Brands LLC
Category: otc | Type: HUMAN OTC DRUG LABEL
Date: 20250521

ACTIVE INGREDIENTS: ACETAMINOPHEN 160 mg/5 mL
INACTIVE INGREDIENTS: ANHYDROUS CITRIC ACID; GLYCERIN; MICROCRYSTALLINE CELLULOSE; CARBOXYMETHYLCELLULOSE SODIUM, UNSPECIFIED; POTASSIUM SORBATE; WATER; SORBITOL SOLUTION; SUCRALOSE; SUCROSE; XANTHAN GUM

TYLENOL For Children Plus Adults

Drug Facts

Active ingredient (in each 5 mL)

Acetaminophen 160 mg

Purpose

Pain reliever/fever reducer

Uses

- temporarily:
  - reduces fever
  - relieves minor aches and pains due to:
    - the common cold
    - flu
    - headache
    - sore throat
    - toothache
    - muscular aches
    - backache
    - minor pain of arthritis
    - premenstrual and menstrual cramps

Warnings

Liver warning

This product contains acetaminophen. Severe liver damage may occur if
■ adult takes more than 4,000 mg of acetaminophen in 24 hours
■ child takes more than 5 doses in 24 hours, which is the maximum daily amount
■ taken with other drugs containing acetaminophen
■ adult has 3 or more alcoholic drinks every day while using this product

Allergy alert: acetaminophen may cause severe skin reactions.
Symptoms may include:
■ skin reddening ■ blisters ■ rash
If a skin reaction occurs, stop use and seek medical help right away.

Sore throat warning

if sore throat is severe, persists for more than 2 days, is accompanied or followed by fever, headache, rash, nausea, or vomiting, consult a doctor promptly.

Do not use

■ with any other drug containing acetaminophen (prescription or nonprescription). If you are not sure whether a drug contains acetaminophen, ask a doctor or pharmacist.

■ if you are allergic to acetaminophen or any of the inactive ingredients in this product

Ask a doctor before use if the user
■ has liver disease
■ is a child with pain of arthritis

Ask a doctor or pharmacist before use if the user is taking the blood thinning drug warfarin

When using this product do not exceed recommended dose (see overdose warning)

Stop use and ask a doctor if
■ pain gets worse or lasts more than 10 days in adults
■ pain gets worse or lasts more than 5 days in children under 12 years
■ fever gets worse or lasts more than 3 days
■ new symptoms occur
■ redness or swelling is present
These could be signs of a serious condition.

PREGNANCY OR BREAST FEEDING

If pregnant or breast-feeding, ask a health professional before use.

Keep out of reach of children.

Overdose warning

In case of overdose, get medical help or contact a Poison Control Center right away. (1-800-222-1222) Quick medical attention is critical for adults as well as for children even if you do not notice any signs or symptoms.

Directions

■ do not give more than directed (see overdose warning)
■ shake well before using
■ mL = milliliter
■ Children 2 years to under 12 years:
■ find right dose on chart below. If possible, use weight to dose; otherwise, use age.
■ remove the child protective cap and squeeze the dose into the dosing cup
■ repeat dose every 4 hours while symptoms last
■ do not take more than 5 times in 24 hours unless directed by a doctor
■ do not take for more than 5 days unless directed by a doctor

Weight (lb) | Age (years) | Dose (mL)*
under 24 | under 2 years | ask a doctor
24-35 lbs | 2-3 years | 5 mL
36-47 lbs | 4-5 years | 7.5 mL
48-59 lbs | 6-8 years | 10 mL
60-71 lbs | 9-10 years | 12.5 mL
72-95 lbs | 11 years | 15 mL

* or as directed by a doctor

■ Adults and children 12 years and over:
■ take 20 mL (2 x 10 mL) every 4 hours while symptoms last. For adult dosing,the dosing cup needs to be filled to 10 mL line twice.
■ do not take more than 5 doses (100 mL) in 24 hours unless directed by a doctor
■ do not take for more than 10 days unless directed by a doctor

Attention: use only enclosed dosing cup specifically designed for use with this product. Do not use any other dosing device.

Other information

- each 5 mL contains: potassium 5 mg
- store between 20-25°C (68-77°F)
- do not use if carton is opened. Do not use if bottle wrap imprinted with “TYLENOL” is broken or missing

Inactive ingredients

anhydrous citric acid, flavors, glycerin, microcrystalline cellulose and carboxymethylcellulose sodium, potassium sorbate, purified water, sorbitol solution, sucralose, sucrose, xanthan gum

Questions or comments?

call 1-877-895-3665 (toll-free) or 215-273-8755 (collect)

RECENT MAJOR CHANGES

dsdsds

PRINCIPAL DISPLAY PANEL

NDC 50580-177-08
Same as Children's TYLENOL ®
with adult dosing

TYLENOL®
FOR CHILDREN
+ ADULTS FAMILY

Acetaminophen (160 mg per 5 mL)
Oral Suspension
Pain Reliever-Fever Reducer

DYE-FREE
Pain+Fever

Ages 2 Years – Adult

FREE OF:
Dyes
Alcohol
Ibuprofen
Aspirin
Parabens
High Fructose
Corn Syrup

8 fl oz (240 mL)
160 mg per 5 mL

Cherry

Flavor